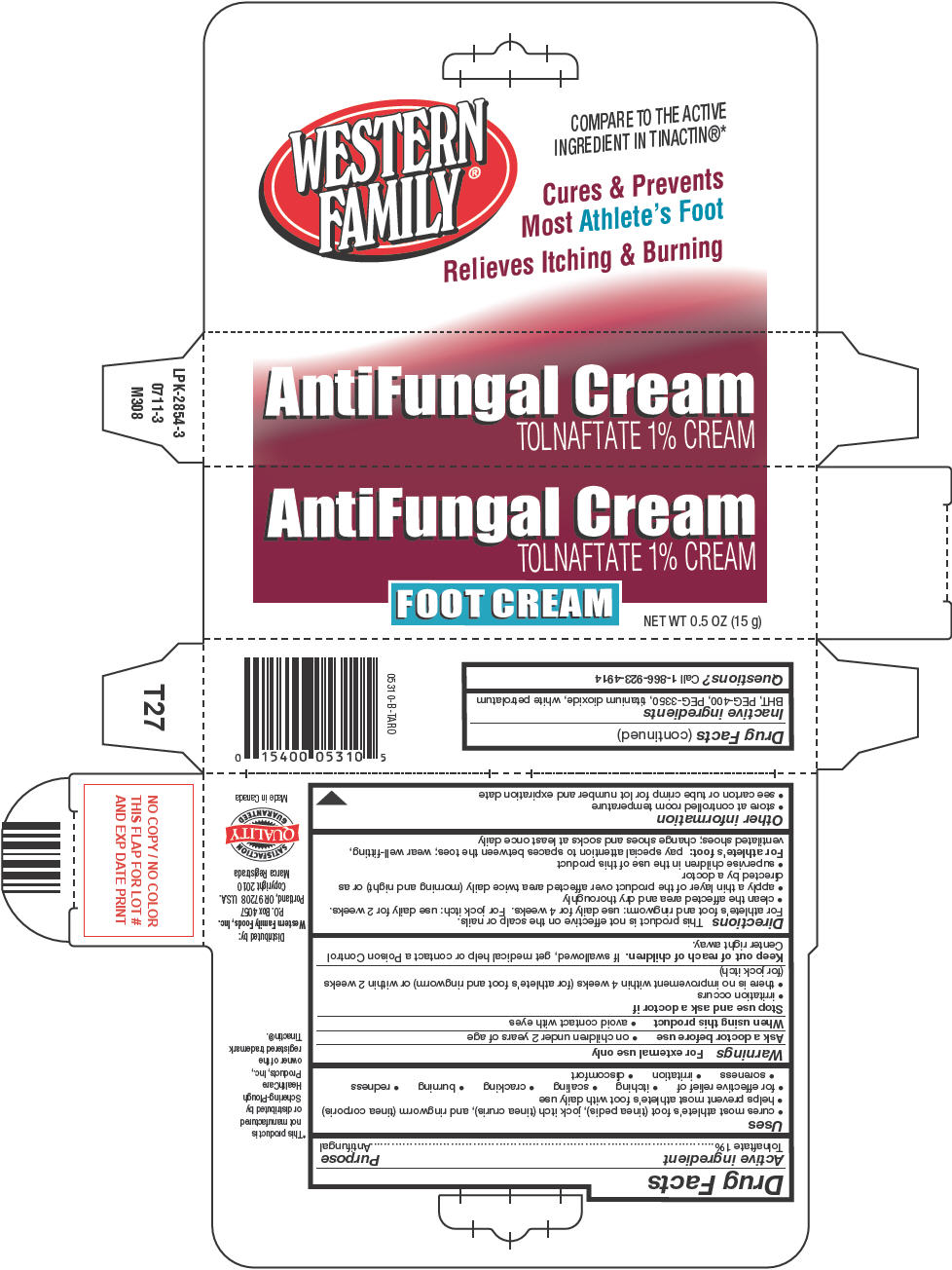 DRUG LABEL: Western Family 
NDC: 55312-020 | Form: CREAM
Manufacturer: Western Family Foods Inc
Category: otc | Type: HUMAN OTC DRUG LABEL
Date: 20130315

ACTIVE INGREDIENTS: Tolnaftate 10 mg/1 g
INACTIVE INGREDIENTS: BUTYLATED HYDROXYTOLUENE; POLYETHYLENE GLYCOL 400; TITANIUM DIOXIDE; PETROLATUM

Western Family®
Antifungal

Drug Facts

Active ingredient

Tolnaftate 1%

Purpose

Antifungal

Uses

- cures most athlete's foot (tinea pedis), jock itch (tinea cruris), and ringworm (tinea corporis)
- helps prevent most athlete's foot with daily use
- for effective relief of
  - itching
  - scaling
  - cracking
  - burning
  - redness
  - soreness
  - irritation
  - discomfort

Warnings

For external use only

Ask a doctor before use

- on children under 2 years of age

When using this product

- avoid contact with eyes

Stop use and ask a doctor if

- irritation occurs
- there is no improvement within 4 weeks (for athlete's foot and ringworm) or within 2 weeks (for jock itch)

Keep out of reach of children. If swallowed, get medical help or contact a Poison Control Center right away.

Directions

This product is not effective on the scalp or nails.

For athlete's foot and ringworm: use daily for 4 weeks. For jock itch: use daily for 2 weeks.

- clean the affected area and dry thoroughly
- apply a thin layer of the product over affected area twice daily (morning and night) or as directed by a doctor
- supervise children in the use of this product

For athlete's foot: pay special attention to spaces between the toes; wear well-fitting, ventilated shoes; change shoes and socks at least once daily

Other information

- store at controlled room temperature
- see carton or tube crimp for lot number and expiration date

Inactive ingredients

BHT, PEG-400, PEG-3350, titanium dioxide, white petrolatum

Questions?

Call 1-866-923-4914

Distributed by:
Western Family Foods, Inc.
P.O. Box 4057
Portland, OR 97208 U.S.A.

PRINCIPAL DISPLAY PANEL - 15 g Tube Carton

AntiFungal Cream
TOLNAFTATE 1% CREAM

FOOT CREAM

NET WT 0.5 OZ (15 g)